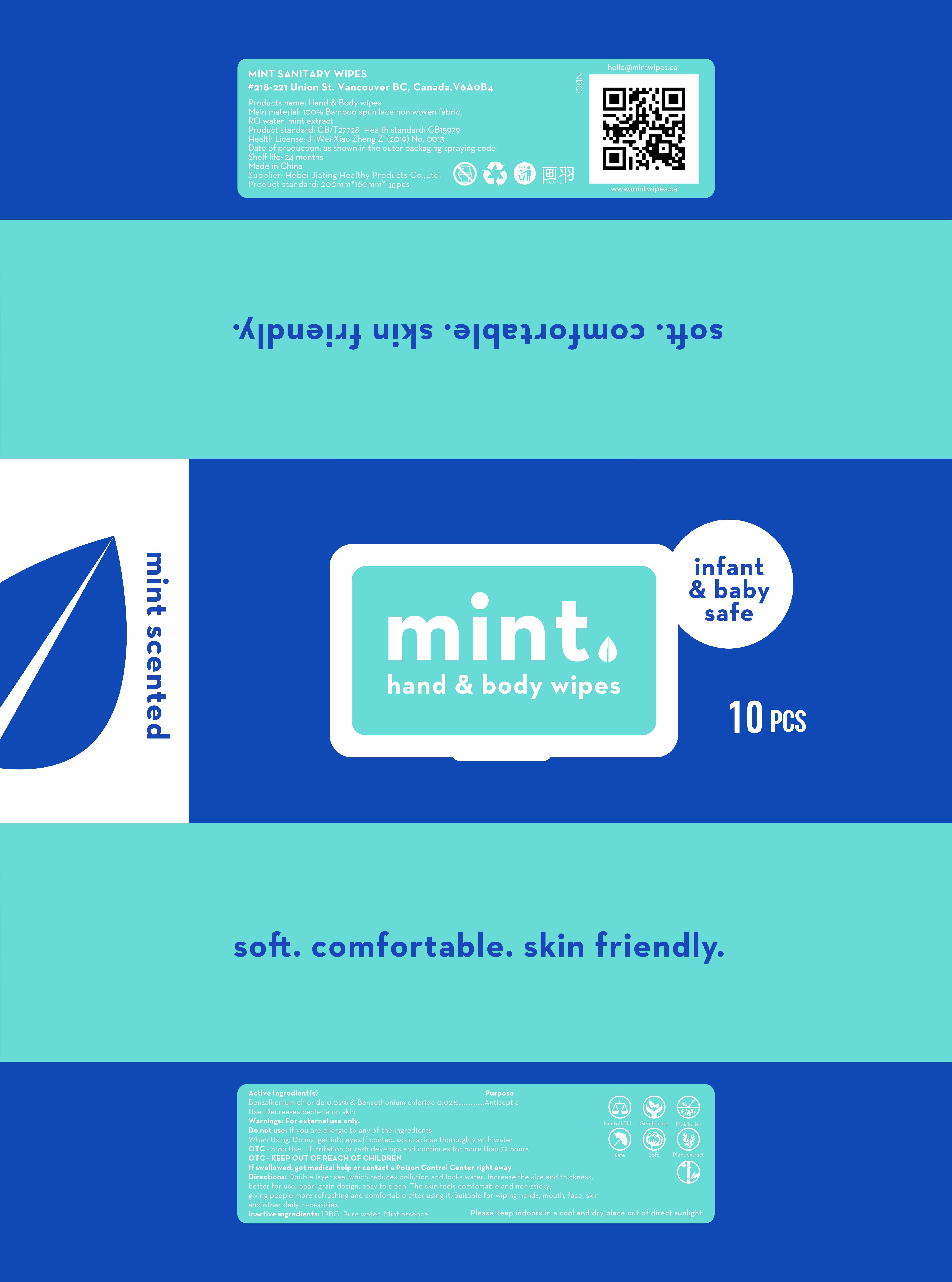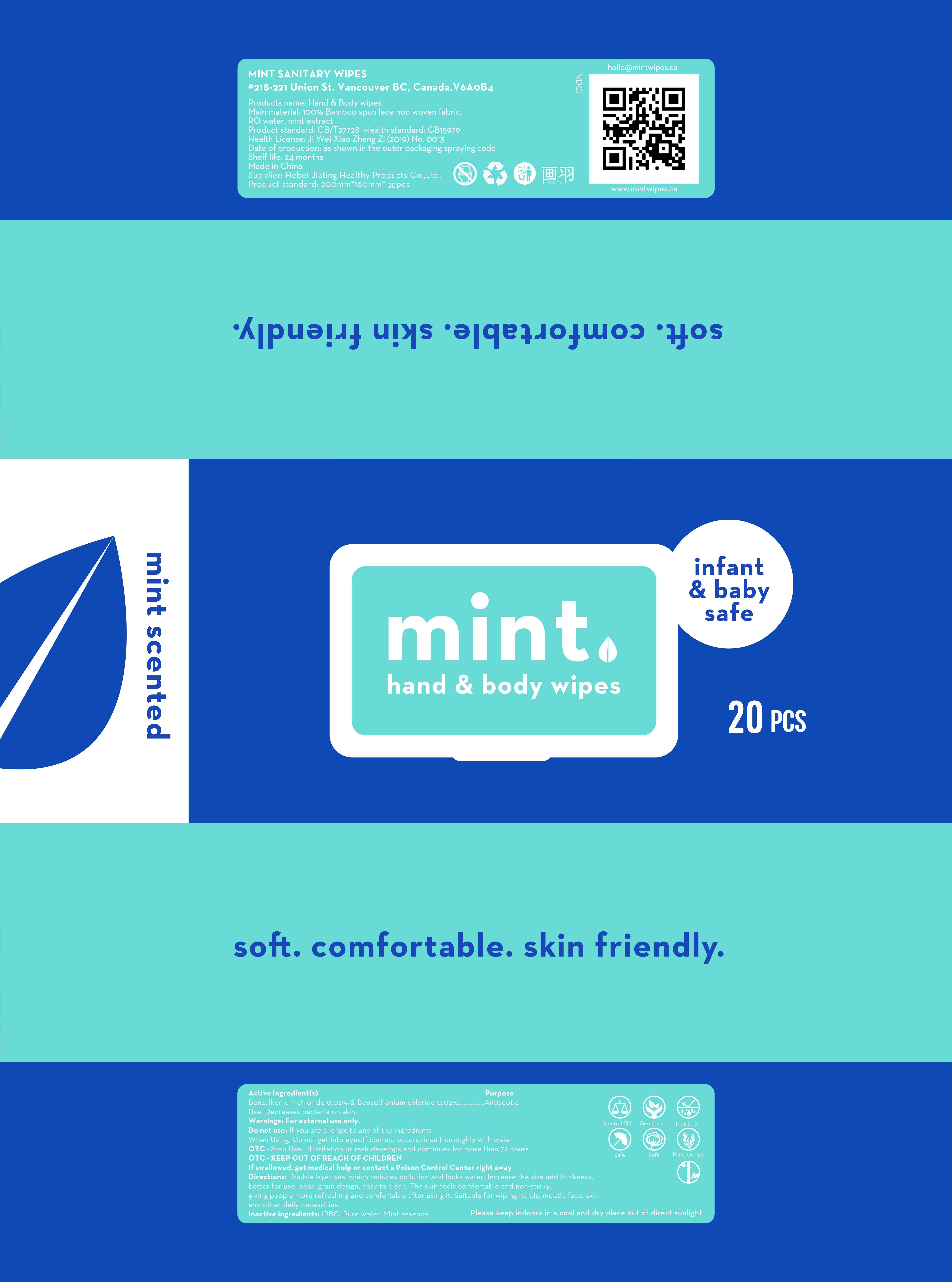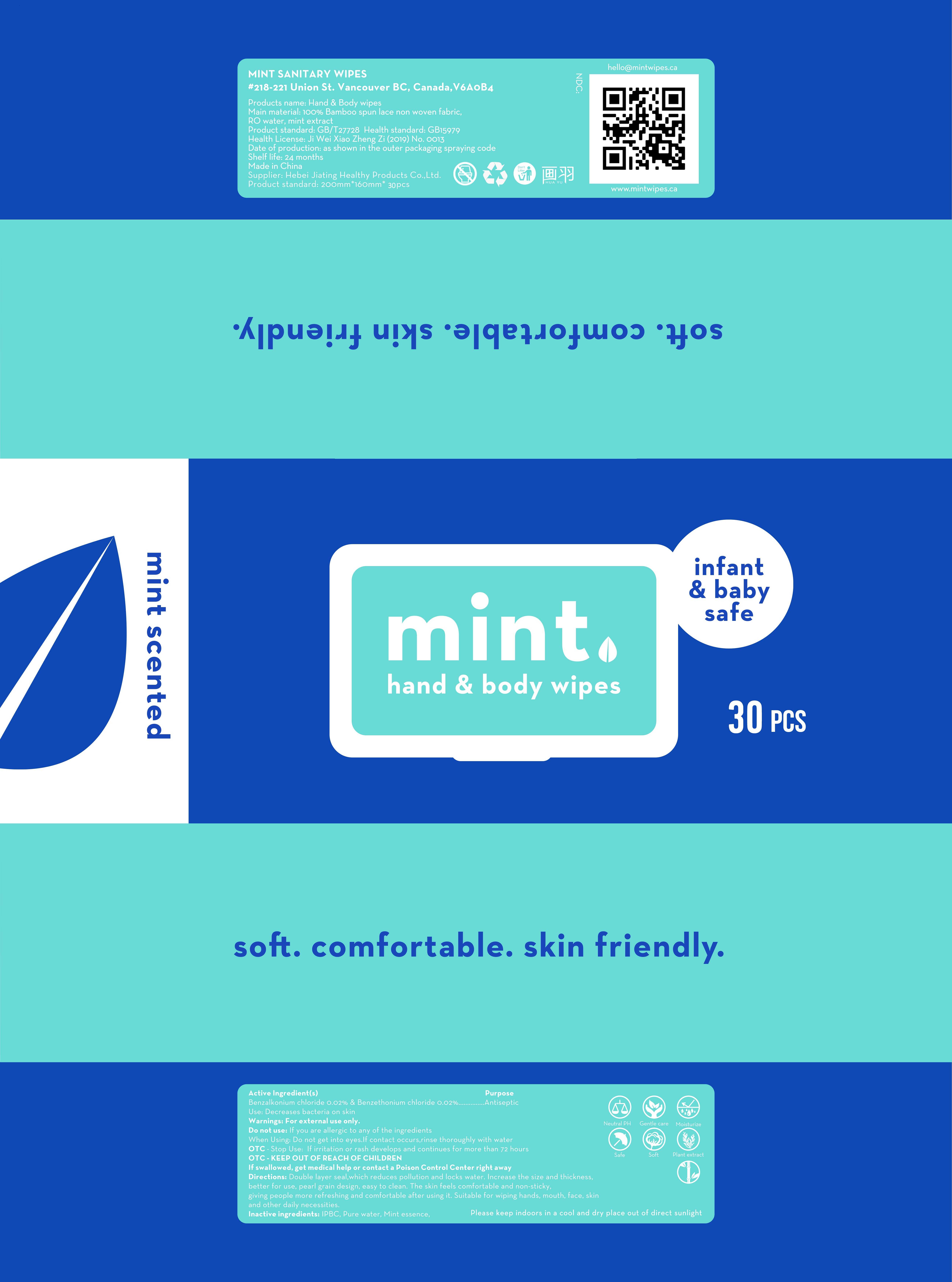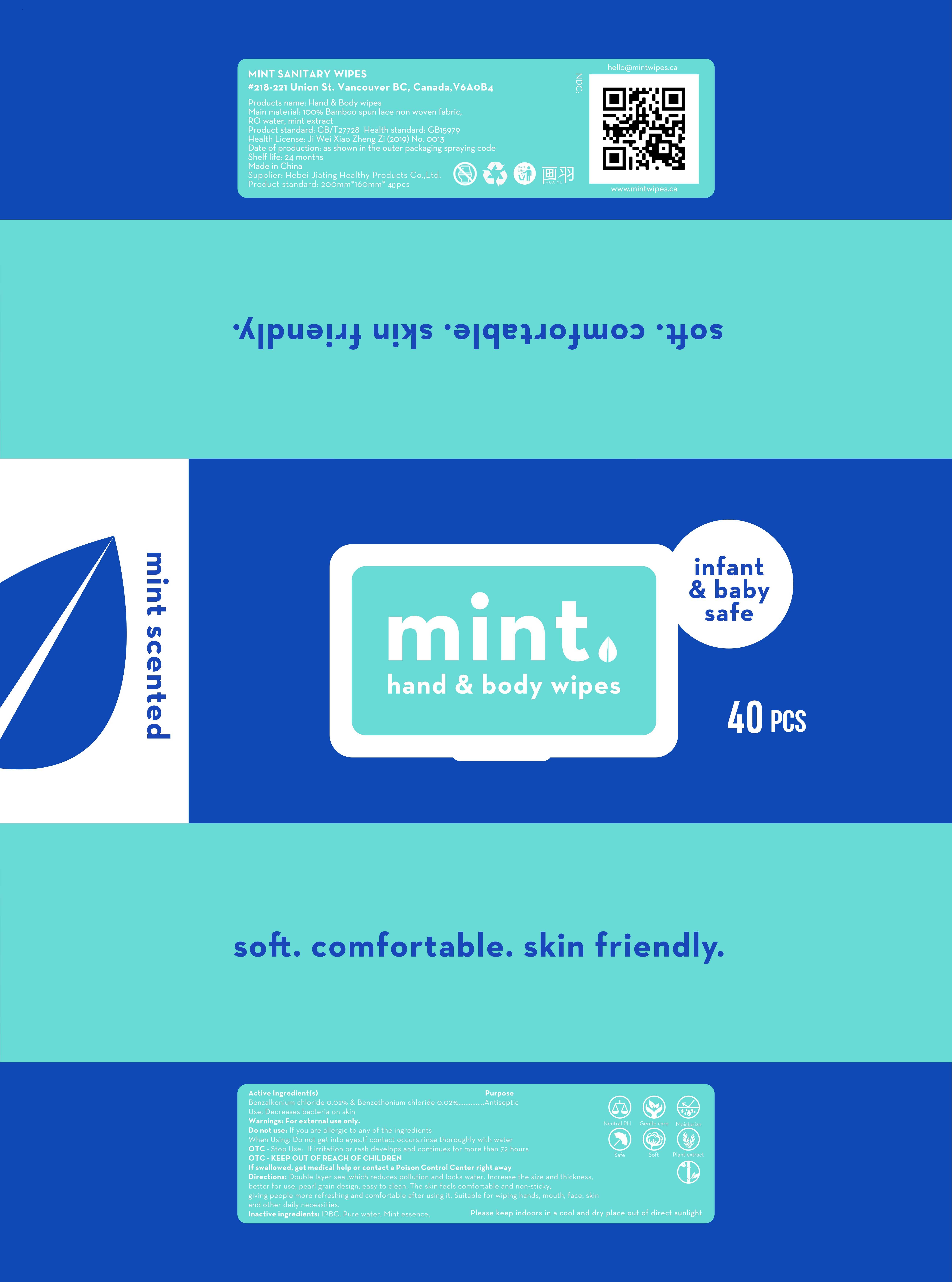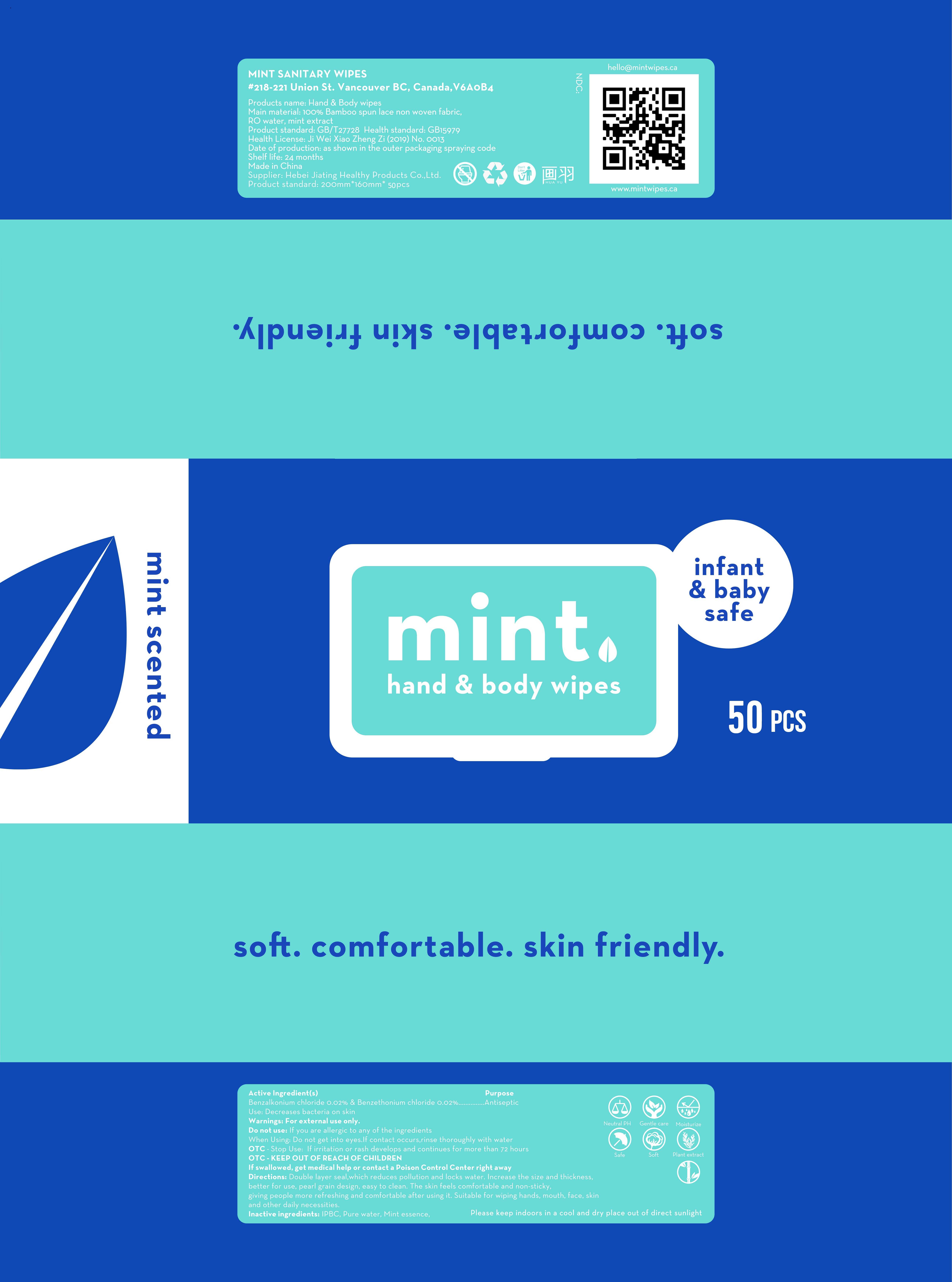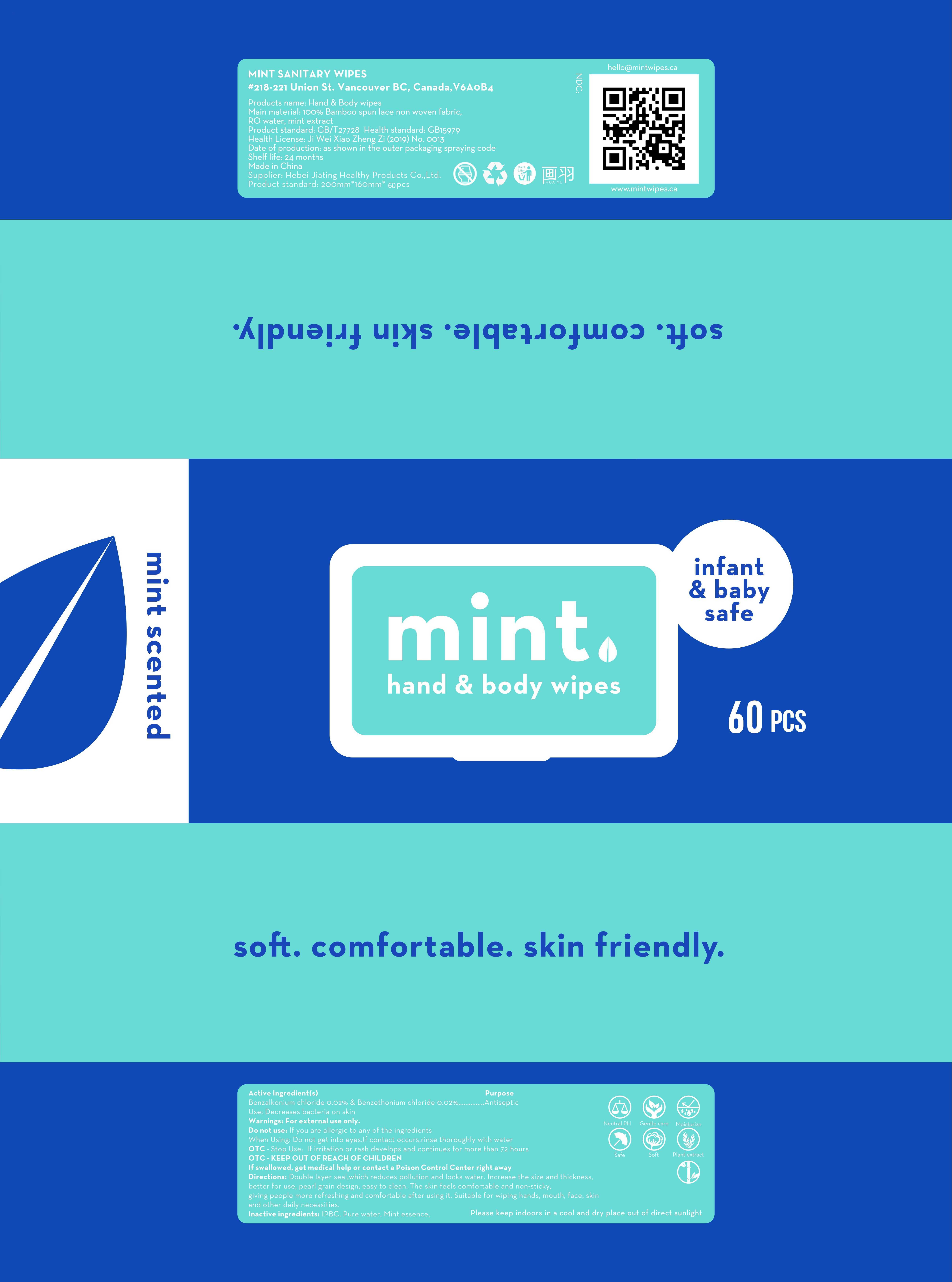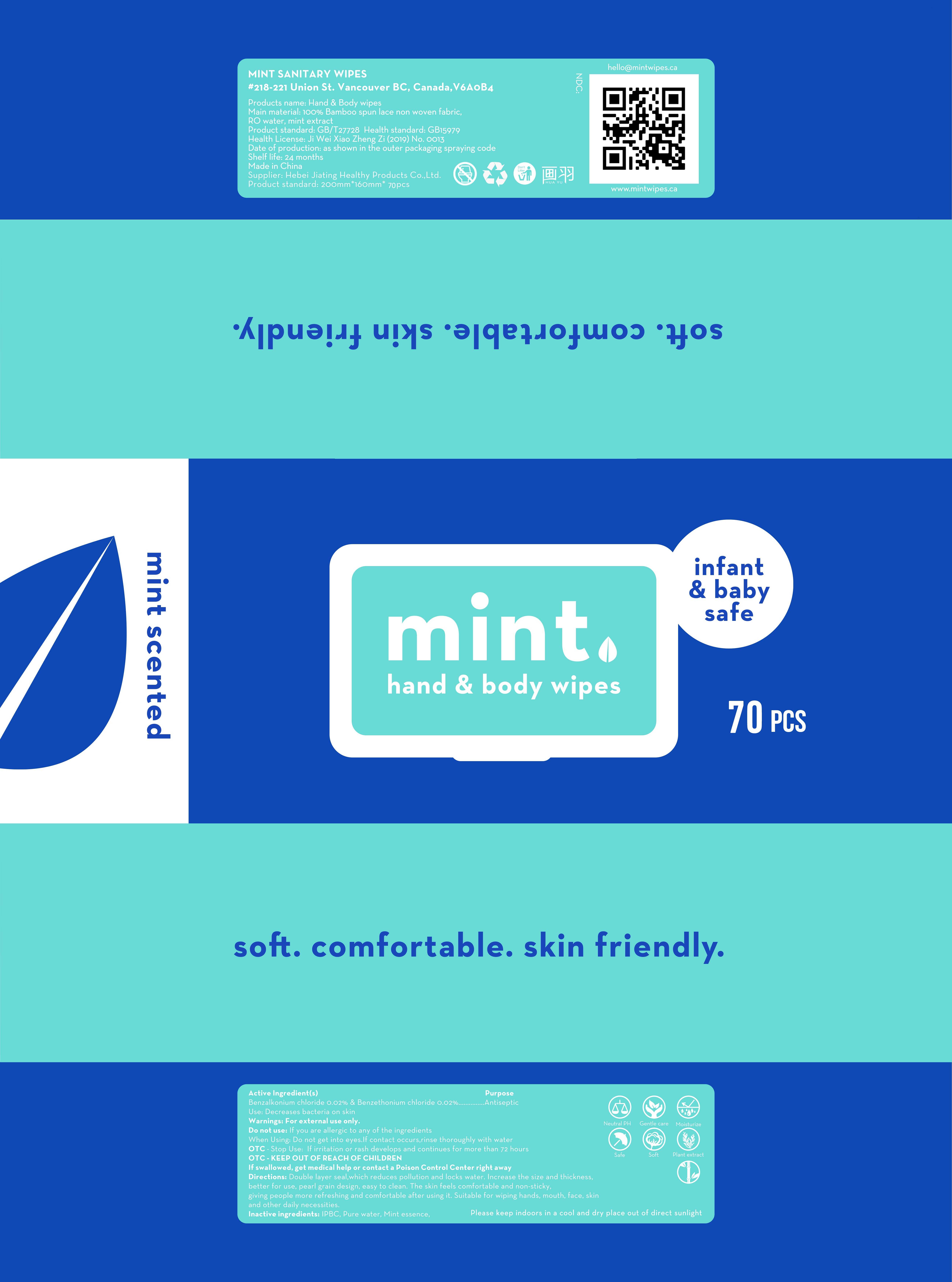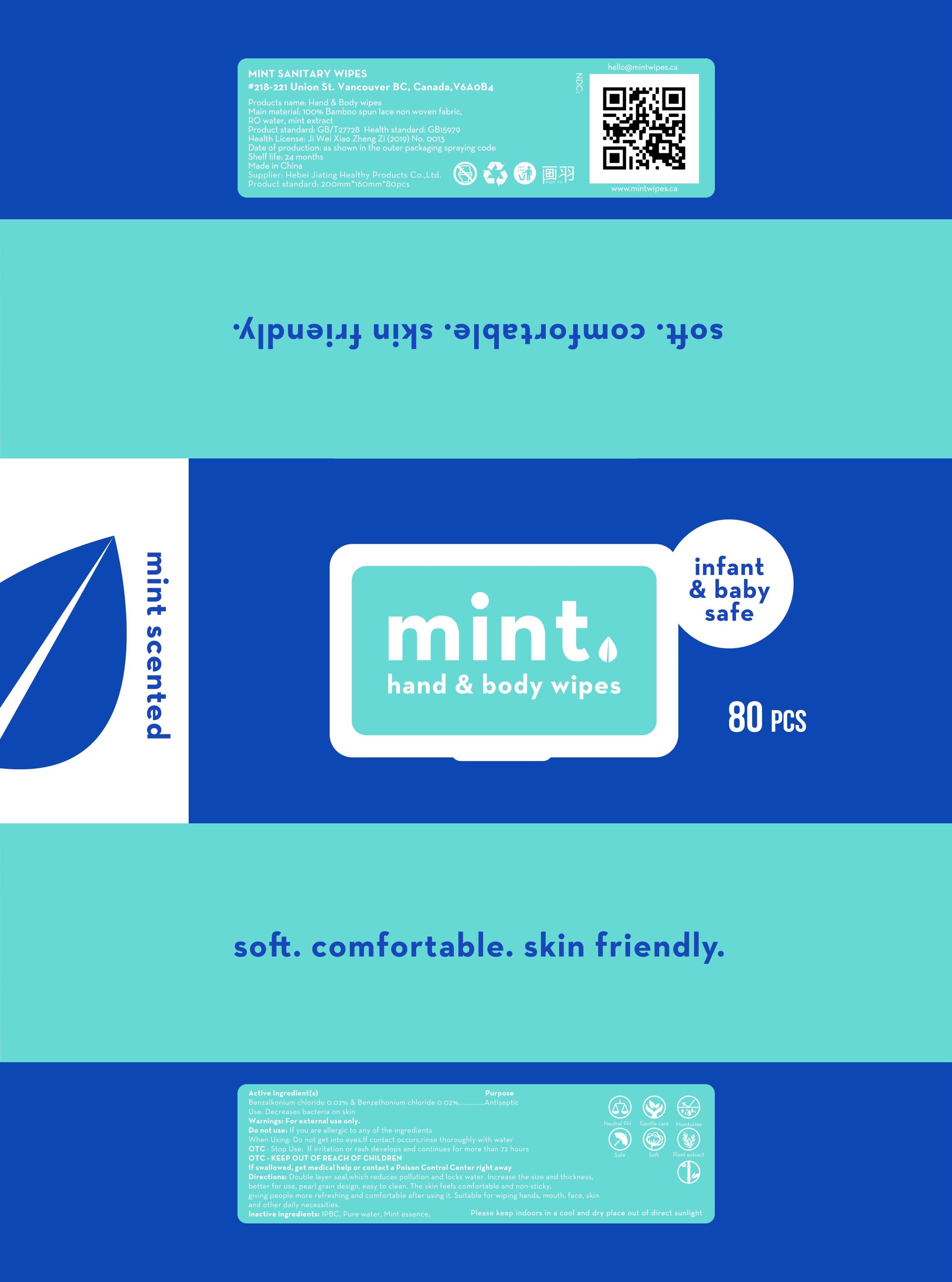 DRUG LABEL: hand body wipe
NDC: 80768-001 | Form: CLOTH
Manufacturer: HEBEI JIATING HEALTH PRODUCT CO.,LTD
Category: otc | Type: HUMAN OTC DRUG LABEL
Date: 20201014

ACTIVE INGREDIENTS: BENZETHONIUM CHLORIDE 0.02 g/100 1; BENZALKONIUM CHLORIDE 0.02 g/100 1
INACTIVE INGREDIENTS: IODOPROPYNYL BUTYLCARBAMATE; MINT; WATER

80768-001
hand body wipe

Active Ingredient(s)

Benzalkonium chloride 0.02%
Benzethonium chloride 0.02%

Purpose

Antiseptic

Use

Decreases bacteria on skin

Warnings

For external use only.

Do not use:
If you are allergic to any of the ingredients

When Using:
Do not get into eyes.If contact occurs.rinse thoroughly with water

O T C - Stop Use:
If irritation or rash develops and continues for more than 72 hours

O T C - K E E P O U T O F REACI-I O F CI-IILDREN
If swallowed, get medical help or contact a Poison Control Center right away

Do not use

If you are allergic to any of the ingredients

WHEN USING

Do not get into eyes.If contact occurs.rinse thoroughly with water

O T C - Stop Use:
If irritation or rash develops and continues for more than 72 hours

O T C - K E E P O U T O F REACI-I O F CI-IILDREN
If swallowed, get medical help or contact a Poison Control Center right away

STOP USE

If irritation or rash develops and continues for more than 72 hours

KEEP OUT OF REACH OF CHILDREN

If swallowed, get medical help or contact a Poison Control Center right away

Directions

Double layer seal.which reduces pollution and locks water. Increase the size and thickness, better for use, pearl grain design, easy to clean. The skin feels comfortable and non-sticky, giving people more refreshing and comfortable after using it. Suitable for wiping hands, mouth, face, skin and other daily necessities.

Other information

/

Inactive ingredients

IPBC, Pure water, Mint essence